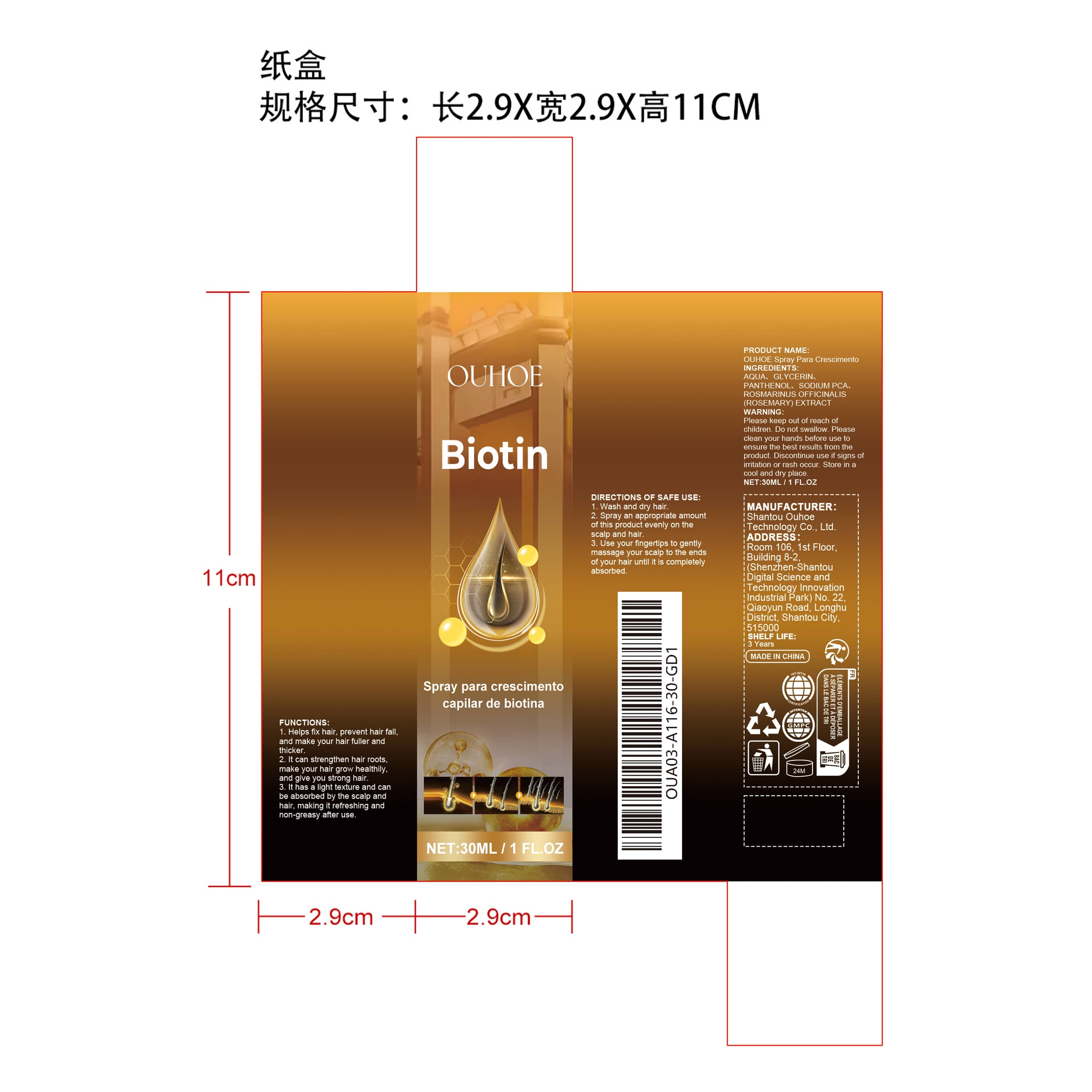 DRUG LABEL: OUHOE Para Crescimento
NDC: 85163-009 | Form: LIQUID
Manufacturer: Shantou Ouhoe Technology Co., Ltd.
Category: otc | Type: HUMAN OTC DRUG LABEL
Date: 20251127

ACTIVE INGREDIENTS: ROSMARINUS OFFICINALIS (ROSEMARY) LEAF OIL 0.006 mg/30 mg
INACTIVE INGREDIENTS: GLYCERIN 1.2 mg/30 mg; AQUA 28.044 mg/30 mg; SODIUM PCA 0.3 mg/30 mg; PANTHENOL 0.45 mg/30 mg

ACTIVE INGREDIENT

ROSMARINUS OFFICINALIS (ROSEMARY) EXTRACT

PURPOSE

1. Helps fix hair, prevent hair fall, and make your hair fuller and thicker.

2. It can strengthen hair roots, make your hair grow healthily, and give you strong hair.

3. It has a light texture and can be absorbed by the scalp and hair, making it refreshing and non-greasy after use.

WHEN USING

1. Wash and dry hair

2. Spray an appropriate amount of this product evenly on the scalp and hair

3. Use your fingertips to gently massage your scalp to the ends of your hair until it is completely absorbed.

WARNINGS

Please keep out of reach of children. Do not swallow.Please clean your hands before use to ensure the best results from the product. Discontinue use if signs of irritation or rash occur. Store in a cool and dry place.

DO NOT USE

Discontinue use if signs of irritation or rash occur.

STOP USE

Discontinue use if signs of irritation or rash occur.

KEEP OUT OF REACH OF CHILDREN

Please keep out of reach of children. Do not swallow.

STORAGE AND HANDLING

Store in a cool and dry place.

INACTIVE INGREDIENT

AQUA、GLYCERIN、PANTHENOL、SODIUM PCA

INDICATIONS AND USAGE

1. Wash and dry hair

2. Spray an appropriate amount of this product evenly on the scalp and hair

3. Use your fingertips to gently massage your scalp to the ends of your hair until it is completely absorbed.

DOSAGE AND ADMINISTRATION

1. Wash and dry hair

2. Spray an appropriate amount of this product evenly on the scalp and hair

3. Use your fingertips to gently massage your scalp to the ends of your hair until it is completely absorbed.